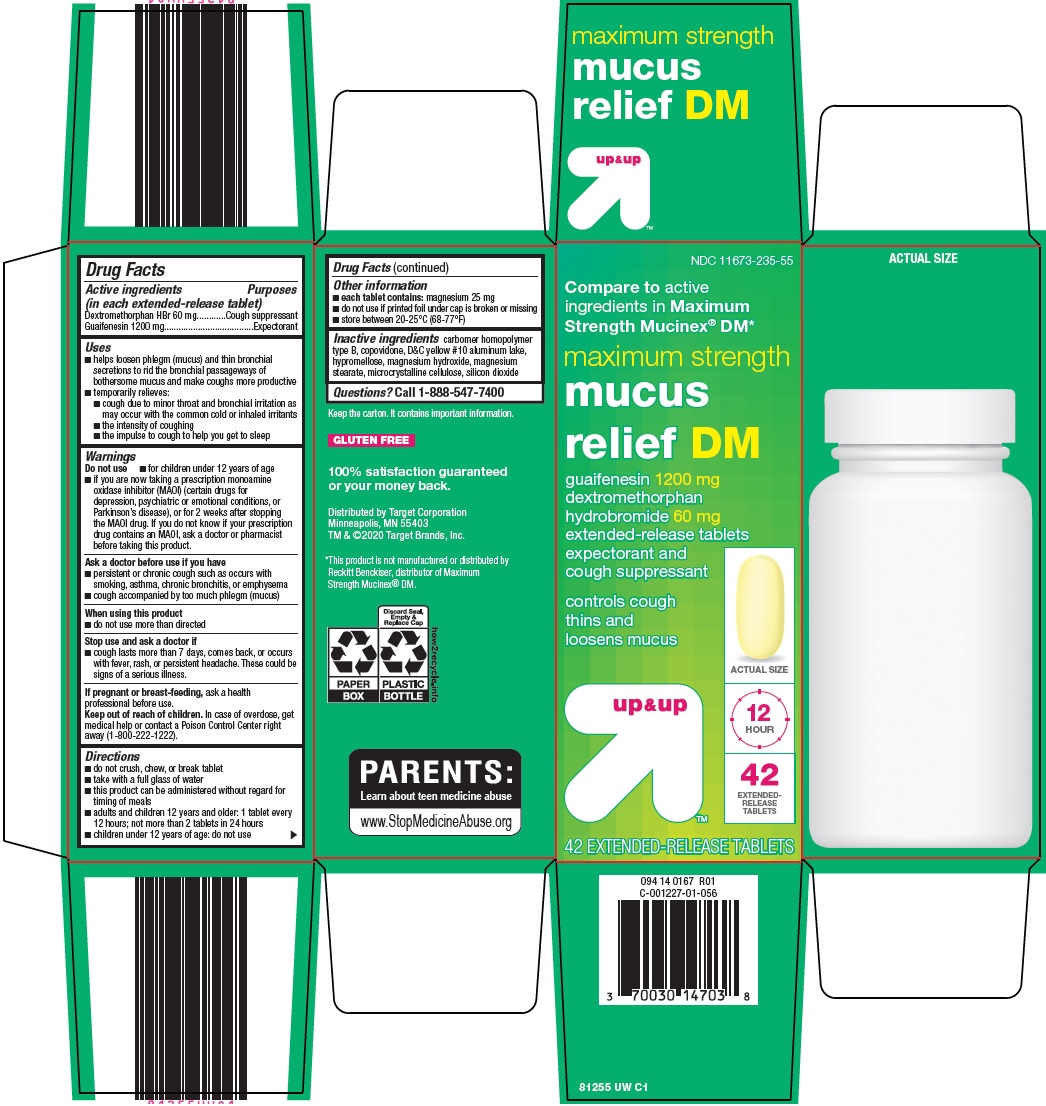 DRUG LABEL: up and up maximum strength mucus relief dm
NDC: 11673-235 | Form: TABLET, EXTENDED RELEASE
Manufacturer: Target Corporation
Category: otc | Type: HUMAN OTC DRUG LABEL
Date: 20260226

ACTIVE INGREDIENTS: GUAIFENESIN 1200 mg/1 1; DEXTROMETHORPHAN HYDROBROMIDE 60 mg/1 1
INACTIVE INGREDIENTS: CARBOMER HOMOPOLYMER TYPE B (ALLYL PENTAERYTHRITOL CROSSLINKED); COPOVIDONE K25-31; D&C YELLOW NO. 10; HYPROMELLOSE, UNSPECIFIED; MAGNESIUM HYDROXIDE; MAGNESIUM STEARATE; MICROCRYSTALLINE CELLULOSE; SILICON DIOXIDE

Target Corporation Maximum Strength Mucus Relief DM Drug Facts

Active ingredients (in each extended-release tablet)

Dextromethorphan HBr 60 mg

Guaifenesin 1200 mg

Purposes

Cough suppressant

Expectorant

Uses

- helps loosen phlegm (mucus) and thin bronchial secretions to rid the bronchial passageways of bothersome mucus and make coughs more productive
- temporarily relieves:
- cough due to minor throat and bronchial irritation as may occur with the common cold or inhaled irritants
- the intensity of coughing
- the impulse to cough to help you get to sleep

Do not use

- for children under 12 years of age
- if you are now taking a prescription monoamine oxidase inhibitor (MAOI) (certain drugs for depression, psychiatric or emotional conditions, or Parkinson’s disease), or for 2 weeks after stopping the MAOI drug. If you do not know if your prescription drug contains an MAOI, ask a doctor or pharmacist before taking this product.

Ask a doctor before use if you have

- persistent or chronic cough such as occurs with smoking, asthma, chronic bronchitis, or emphysema
- cough accompanied by too much phlegm (mucus)

When using this product

- do not use more than directed

Stop use and ask a doctor if

- cough lasts more than 7 days, comes back, or occurs with fever, rash, or persistent headache. These could be signs of a serious illness.

If pregnant or breast-feeding,

ask a health professional before use.

Keep out of reach of children.

In case of overdose, get medical help or contact a Poison Control Center right away (1-800-222-1222).

Directions

- do not crush, chew, or break tablet
- take with a full glass of water
- this product can be administered without regard for timing of meals
- adults and children 12 years and older: 1 tablet every 12 hours; not more than 2 tablets in 24 hours
- children under 12 years of age: do not use

Other information

- each tablet contains: magnesium 25 mg
- do not use if printed foil under cap is broken or missing
- store between 20-25°C (68-77°F)

Inactive ingredients

carbomer homopolymer type B, copovidone, D&C yellow #10 aluminum lake, hypromellose, magnesium hydroxide, magnesium stearate, microcrystalline cellulose, silicon dioxide

Questions?

Call 1-888-547-7400

Package/Label Principal Display Panel

Compare to active ingredients in Maximum Strength Mucinex® DM

maximum strength mucus relief DM

guaifenesin 1200 mg

dextromethorphan hydrobromide 60 mg

extended-release tablets

expectorant and cough suppressant

controls cough

thins and loosens mucus

ACTUAL SIZE

12 HOUR

42 EXTENDED-RELEASE TABLETS

42 EXTENDED-RELEASE TABLETS